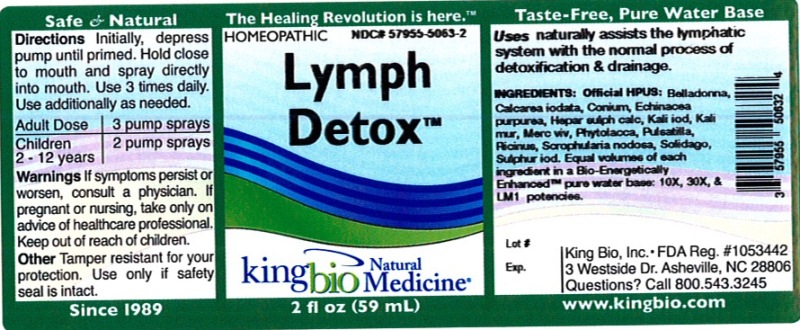 DRUG LABEL: Lymph Detox
NDC: 57955-5063 | Form: LIQUID
Manufacturer: King Bio Inc.
Category: homeopathic | Type: HUMAN OTC DRUG LABEL
Date: 20120614

ACTIVE INGREDIENTS: ATROPA BELLADONNA 10 [hp_X]/59 mL; CALCIUM IODIDE 10 [hp_X]/59 mL; CONIUM MACULATUM FLOWERING TOP 10 [hp_X]/59 mL; ECHINACEA PURPUREA 10 [hp_X]/59 mL; CALCIUM SULFIDE 10 [hp_X]/59 mL; POTASSIUM IODIDE 10 [hp_X]/59 mL; POTASSIUM CHLORIDE 10 [hp_X]/59 mL; MERCURY 10 [hp_X]/59 mL; PHYTOLACCA AMERICANA ROOT 10 [hp_X]/59 mL; PULSATILLA VULGARIS 10 [hp_X]/59 mL; RICINUS COMMUNIS SEED 10 [hp_X]/59 mL; SCROPHULARIA NODOSA 10 [hp_X]/59 mL; SOLIDAGO VIRGAUREA FLOWERING TOP 10 [hp_X]/59 mL; SULFUR IODIDE 10 [hp_X]/59 mL
INACTIVE INGREDIENTS: WATER

Lymph Detox

Active Ingredients

Official HPUS: Belladonna, Calcarea iodata, Conium maculatum, Echinacea purpurea, Hepar sulphuris calcareum, Kali iodatum, Kali muriaticum, Mercurius vivus, Phytolacca decandra, Pulsatilla, Ricinus communis, Scrophularia nodosa, Solidago virgaurea, and sulphur iodatum.

Reference image lymph detox.jpg

Inactive Ingredient

Equal volumes of each ingredient in a Bio-Energetically Enhanced pure water base: 10X, 30X, and LM1 potencies.

Reference image lymph detox.jpg

Dosage and Administration

Directions: Initially, depress pump until primed. Hold close to mouth and spray directly into mouth. Use 3 times daily. Use additionally as needed.

Adult Dose 3 pump sprays

Children 2-12 years 2 pump sprays

Reference image lymph detox.jpg

Purpose

Uses naturally assists the lymphatic system with the normal process of detoxification and drainage.

Reference image lymph detox.jpg

Warnings

If symptoms persist or worsen, consult a physician. If pregnant or nursing, take only on advice of healthcare professional. Keep out of reach of children.

Other: Tamper resistant for your protection. Use only if safety seal is intact.

Reference image lymph detox.jpg

Keep out of reach of children.

Reference image lymph detox.jpg

Indications and Usage

Uses naturally assists the lymphatic system with the normal process of detoxification and drainage.

Reference image lymph detox.jpg

PACKAGE LABEL

King Bio Inc.

3 Westside Drive

Asheville, NC 28806

Questions? Call 800.543.3245

www.kingbio.com